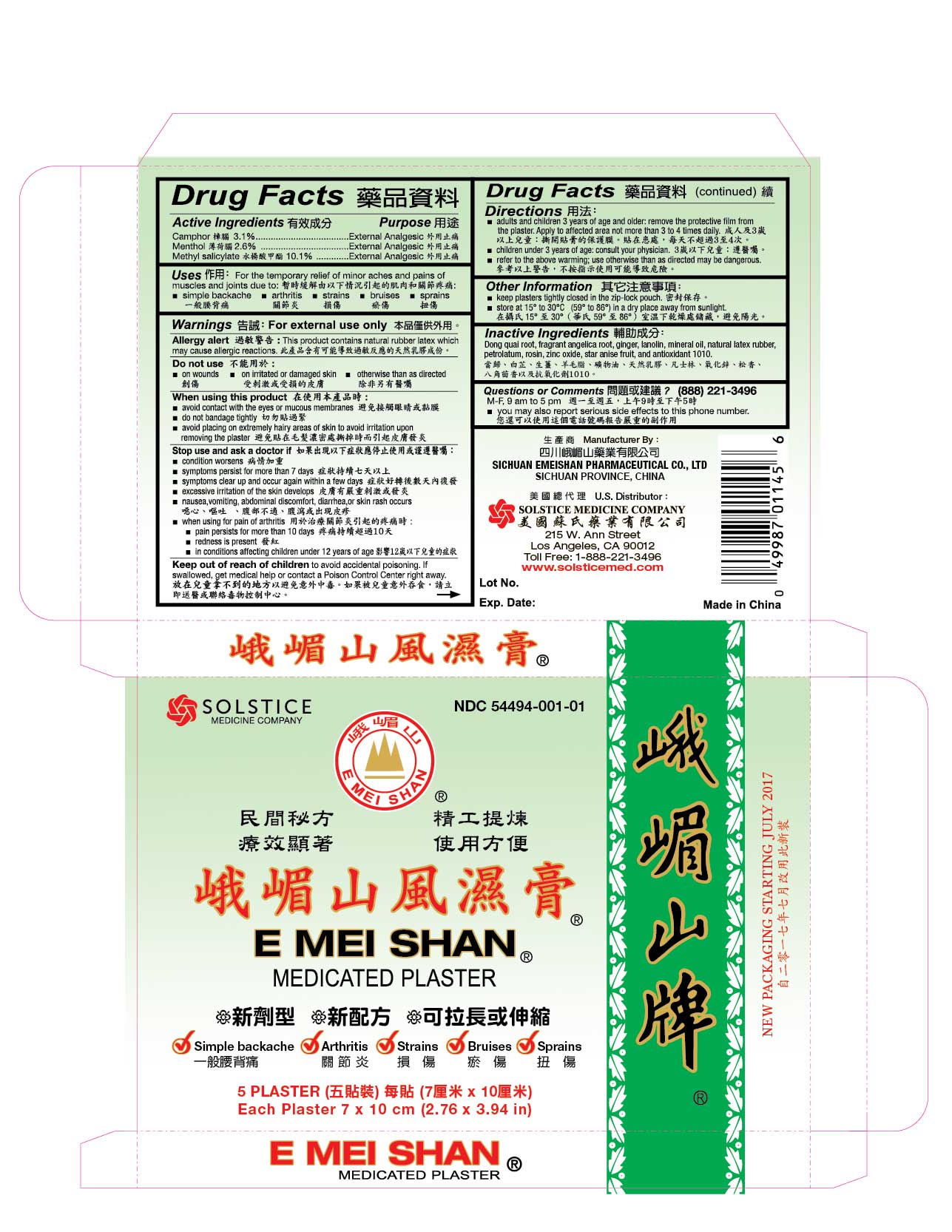 DRUG LABEL: E MEI SHAN MEDICATED
NDC: 54494-001 | Form: PLASTER
Manufacturer: SICHUAN EMEISHAN PHARMACEUTICAL CO., LTD.
Category: otc | Type: HUMAN OTC DRUG LABEL
Date: 20170811

ACTIVE INGREDIENTS: CAMPHOR (SYNTHETIC) 36 mg/1 1; MENTHOL 30 mg/1 1; METHYL SALICYLATE 119 mg/1 1
INACTIVE INGREDIENTS: ANGELICA SINENSIS ROOT; ANGELICA DAHURICA ROOT; GINGER; LANOLIN; MINERAL OIL; NATURAL LATEX RUBBER; PETROLATUM; ZINC OXIDE; ROSIN; STAR ANISE FRUIT; PENTAERYTHRITOL TETRAKIS(3-(3,5-DI-TERT-BUTYL-4-HYDROXYPHENYL)PROPIONATE)

Drug Facts

Active Ingredients
Camphor 3.1%
Menthol 2.6%
Methyl Salicylate 10.1%

Purpose
External Analgesic

Uses
For the temporary relief of minor aches and pains of muscles and joints due to:
■ simple backache ■ arthritis ■ strains ■ bruises ■ sprains

Warnings
For external use only
Allergy alert: This product contains natural rubber latex which may cause allergic reactions

Do not use
■ on irritated or damaged skin ■ on wounds ■ otherwise than as directed

When using this product
■ avoid contact with the eyes or mucous membranes
■ do not bandage tightly
■ avoid placing on extremely hairy areas of skin to avoid irritation upon removing the plaster

Stop use and ask a doctor if
■ condition worsens
■ symptoms persist for more than 7 days
■ symptoms clear up and occur again within a few days
■ excessive irritation of the skin develops
■ nausea, vomiting, abdominal discomfort, diarrhea, or skin rash occurs
■ when using for pain of arthritis:
■ pain persists for more than 10 days ■ redness is present
■ in conditions affecting children under 12 years of age

Keep out of reach of children to avoid accidental poisoning.
If swallowed, get medical help or contact a Poison Control Center right away.

Directions
■ adults and children 3 years of age and older: remove the protective film from the plaster. Apply to affected area not more than 3 to 4 times daily.
■ children under 3 years of age: consult your physician
■ refer to the above warnings; use otherwise than as directed may be dangerous

Other information
■ keep plasters tightly closed in the zip-lock pouch
■ store at 15º to 30º C (59º to 86º F) in a dry place away from sunlight

Inactive ingredients
Dong quai root, fragrant angelica root, ginger, lanolin, mineral oil, natural latex rubber, petrolatum, rosin, zinc oxide, star anise fruit, and antioxidant 1010.

Questions or comments?
(888) 221-3496 M-F 9 am to 5 pm
■ you may also report serious side effects to this phone number

PACKAGE LABEL

Principal Display Panel
EXTERNAL ANALGESIC
NDC 54494-001-01
E MEI SHAN MEDICATED PLASTER
■ Simple backache ■ Arthritis ■ Strains ■ Bruises ■ Sprains
5 PLASTERS
Each plaster 7 x 10 cm (2.76 x 3.94 Inches)